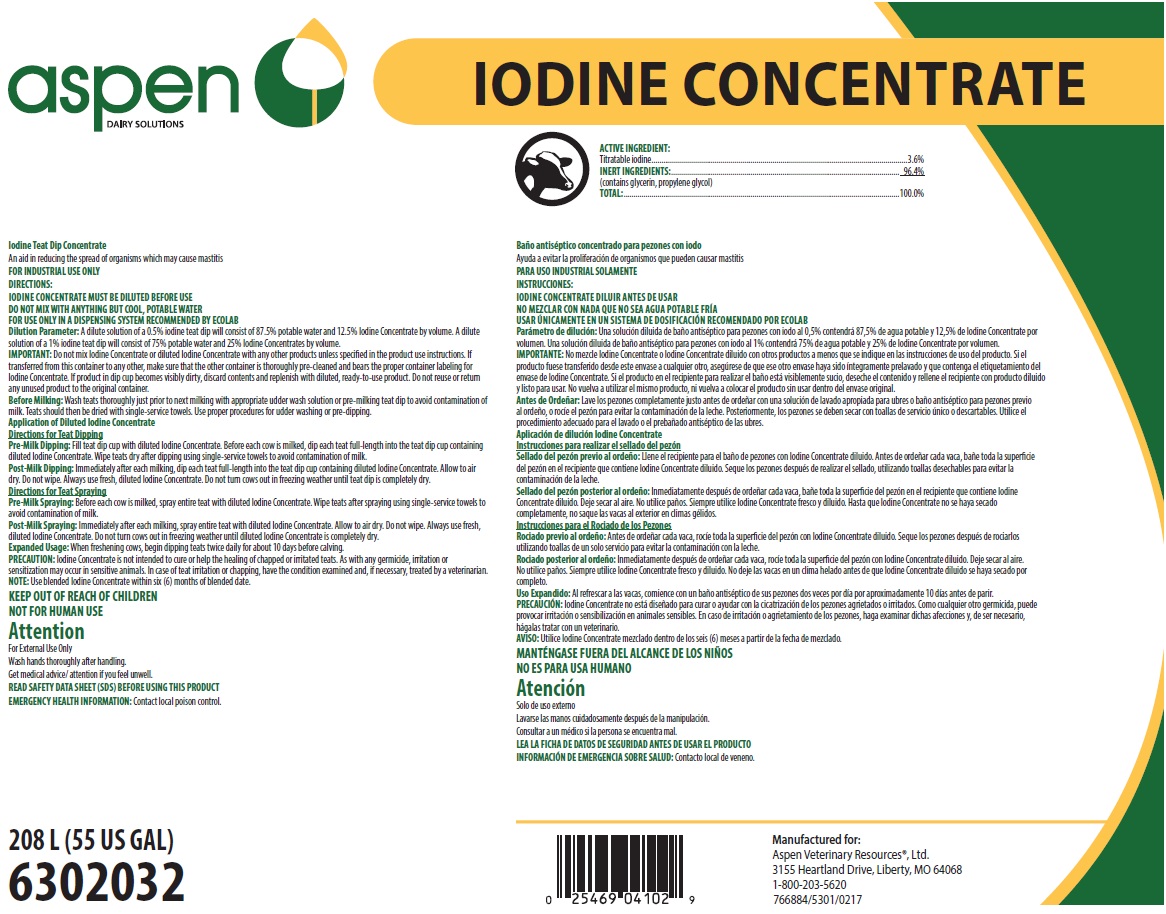 DRUG LABEL: ASPEN IODINE CONC
NDC: 46066-412 | Form: SOLUTION
Manufacturer: Aspen Veterinary Resources
Category: animal | Type: OTC ANIMAL DRUG LABEL
Date: 20250710

ACTIVE INGREDIENTS: IODINE 36 mg/1 mL
INACTIVE INGREDIENTS: GLYCERIN; PROPYLENE GLYCOL

SAFE HANDLING WARNING

FOR INDUSTRIAL USE ONLY

KEEP OUT OF REACH OF CHILDREN

NOT FOR HUMAN USE

Attention

For External Use Only

Wash hands thoroughly after handling.

Get medical advice/attention if you feel unwell.

DIRECTIONS:

IODINE CONCENTRATE MUST BE DILUTED BEFORE USE

DO NOT MIX WITH ANYTHING BUT COOL, POTABLE WATER

FOR USE ONLY IN A DISPENSING SYSTEM RECOMMENDED BY ECOLAB

Dilution Parameter: A dilute solution of a 0.5% iodine teat dip will consist of 87.5% potable water and 12.5% Iodine Concentrate by volume. A dilute solution of a 1% iodine teat dip will consist of 75% potable water and 25% Iodine Concentrates by volume.

IMPORTANT: Do not mix Iodine Concentrate or diluted Iodine Concentrate with any other products unless specified in the product use instructions. If transferred from this container to any other, make sure that the other container is thoroughly pre-cleaned and bears the proper container labeling for Iodine Concentrate. If product in dip cup becomes visibly dirty, discard contents and replenish with diluted, ready-to-use product. Do not reuse or return any unused product to the original container.

Before Milking: Wash teats thoroughly just prior to next milking with appropriate udder wash solution or pre-milking teat dip to avoid contamination of milk. Teats should then be dried with single-service towels. Use proper procedures for udder washing or pre-dipping.

Application of Diluted Iodine Concentrate

Directions for Teat Dipping

Pre-Milk Dipping: Fill teat dip cup with diluted Iodine Concentrate. Before each cow is milked, dip each teat full-length into the teat dip cup containing diluted Iodine Concentrate. Wipe teats dry after dipping using single-service towels to avoid contamination of milk.

Post-Milk Dipping: Immediately after each milking, dip each teat full-length into the teat dip cup containing diluted Iodine Concentrate. Allow to air dry. Do not wipe. Always use fresh, diluted Iodine Concentrate. Do not turn cows out in freezing weather until teat dip is completely dry.

Directions for Teat Spraying

Pre-Milk Spraying: Before each cow is milked, spray entire teat with diluted Iodine Concentrate. Wipe teats after spraying using single-service towels to avoid contamination of milk.

Post-Milk Spraying: Immediately after each milking, spray entire teat with diluted Iodine Concentrate. Allow to air dry. Do not wipe. Always use fresh, diluted Iodine Concentrate. Do not turn cows out in freezing weather until diluted Iodine Concentrate is completely dry.

Expanded Usage: When freshening cows, begin dipping teats twice daily for about 10 days before calving.

PRECAUTION: Iodine Concentrate is not intended to cure or help the healing of chapped or irritated teats. As with any germicide, irritation or sensitization may occur in sensitive animals. In case of teat irritation or chapping, have the condition examined and, if necessary, treated by a veterinarian.

NOTE: Use blended Iodine Concentrate within six (6) months of blended date.

OTHER SAFETY INFORMATION

READ SAFETY DATA SHEET (SDS) BEFORE USING THIS PRODUCT

EMERGENCY HEALTH INFORMATION: Contact local poison control.

Representative label and principal display panel

aspen DAIRY SOLUTIONS

IODINE CONCENTRATE

ACTIVE INGREDIENT

Titratable Iodine................3.6%

INERT INGREDIENTS:........96.4%

(contains glycerin, propylene glycol)

TOTAL:.......................100.0%

Iodine Teat Dip Concentrate

An aid in reducing the spread of organisms which may cause mastitis.

208 L (55 US GAL)

6302032

Manufactured for:

Aspen Veterinary Resources®, Ltd. 3155 Heartl1-and Drive, Liberty, MO 64068

1-800-203-5620

766884/5301/0217